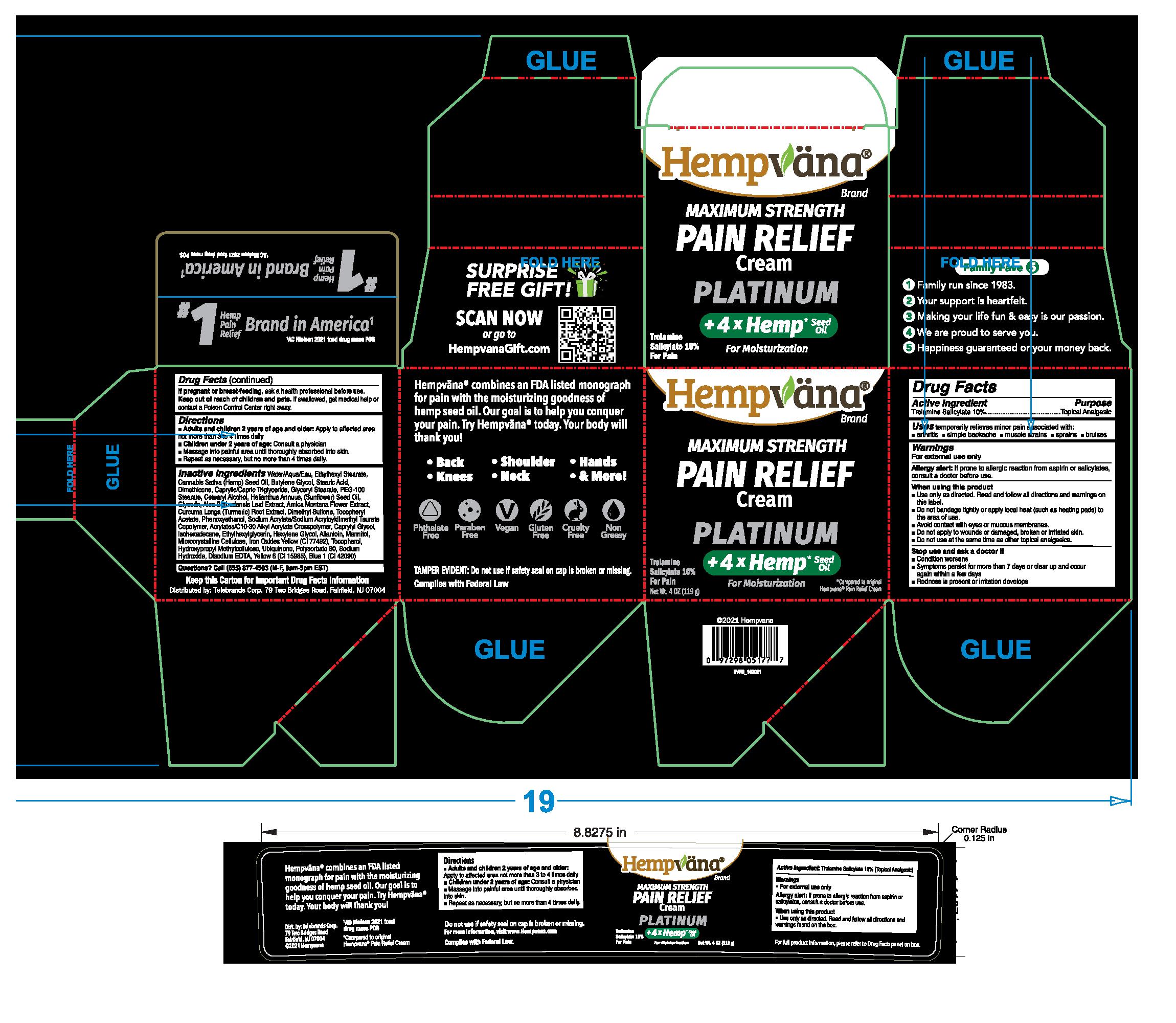 DRUG LABEL: Hempvana Maximum Strength Pain Relief - Platinum
NDC: 73287-021 | Form: CREAM
Manufacturer: TELEBRANDS CORP
Category: otc | Type: HUMAN OTC DRUG LABEL
Date: 20241120

ACTIVE INGREDIENTS: TROLAMINE SALICYLATE 10 g/100 g
INACTIVE INGREDIENTS: ARNICA MONTANA FLOWER; TURMERIC; DIMETHYL SULFONE; .ALPHA.-TOCOPHEROL ACETATE; PHENOXYETHANOL; HYPROMELLOSE, UNSPECIFIED; POLYSORBATE 80; FD&C YELLOW NO. 6; EDETATE DISODIUM ANHYDROUS; UBIDECARENONE; ALLANTOIN; ETHYLHEXYL STEARATE; STEARIC ACID; CARBOMER INTERPOLYMER TYPE A (ALLYL SUCROSE CROSSLINKED); CAPRYLYL GLYCOL; MANNITOL; MICROCRYSTALLINE CELLULOSE; GLYCERYL MONOSTEARATE; CETOSTEARYL ALCOHOL; DIMETHICONE; MEDIUM-CHAIN TRIGLYCERIDES; SUNFLOWER OIL; SODIUM ACRYLATE/SODIUM ACRYLOYLDIMETHYLTAURATE COPOLYMER (4000000 MW); BUTYLENE GLYCOL; FERRIC OXIDE YELLOW; TOCOPHEROL; GLYCERIN; ISOHEXADECANE; ETHYLHEXYLGLYCERIN; SODIUM HYDROXIDE; FD&C BLUE NO. 1; HEXYLENE GLYCOL; WATER; CANNABIS SATIVA SEED OIL; PEG-100 STEARATE; ALOE VERA LEAF

Hempvana Maximum Strength Pain Relief Cream - Platinum

Active ingredient

Trolamine Salicylate 10%

Purpose

Trolamine Salicylate 10%..........Topical Analgesic

Uses

temporarily relieves minor pain associated with:

- arthritis
- simple backache
- muscle strains
- sprains
- bruises

Warnings

For external use only

Allergy alert:If prone to allergic reaction from aspirin or salicylates, consult a doctor before use.

When using this product

- Use only as directed. Read and follow all directions and warnings on this label.
- Do not bandage tightly or apply local heat (such as heating pads) to the area of use.
- Avoid contact with eyes or mucous membranes.
- Do not apply to wounds or damaged, broken or irritated skin.
- Do not use at the same time as other topical analgesics.

Stop use and ask a doctor if

- Condition worsens
- Symptoms persist for more than 7 days or clear up and occur again within a few days
- Redness is present or irritation develops

PREGNANCY OR BREAST FEEDING

If pregnant or breast-feeding,ask a health professional before use.

Keep out of reach of children and pets.If swallowed, get medical help or contact a Poison Control Center right away.

Directions

- Adults and children 2 years of age and older:Apply to affected area not more than 3 to 4 times daily
- Children under 2 years of age:Consult a physician
- Massage into painful area until thoroughly absorbed into skin.
- REpeat as necessary, but no more than 4 times daily.

Inactive ingredients

Water/Aqua/Eau, Ethylhexyl Stearate, Cannabis Sativa (Hemp) Seed Oil, Butylene Glycol, Stearic Acid, DImethicone, Caprylic/Capric Trigylceride, Glyceryl Stearate, PEG-100 Stearate, Cetearyl Alcohol, Helianthus Annuus (Sunflower) Seed Oil, Glycerin, Aloe Barbadensis Leaf Extract, Arnica Montana Flower Extract, Curcuma Longa (Turmeric) Root Extract, Dimethyl Sulfone, Tocopheryl Acetate, Phenoxyethanol, Sodium Acrylate/Sodium Acryloyldimethyl Taurate Copolymer, Acrylates/C10-30 Alkyl Acrylate Crosspolymer, Caprylyl Glycol, Isohexadecane, Ethylhexylglycerin, Hexylene Glycol, Allantoin, Mannitol, Microcrystalline Cellulose, Iron Oxides Yellow (CI 77492), Tocopherol, Hydroxypropyl Methylcellulose, Ubiquinone, Polysorbate 80, Sodium Hydroxide, Disodium EDTA, Yellow 6 (CI 15985), Blue 1 (CI 42090)

Questions?

Call (855) 877-4503 (M-F, 9am-5pm EST)

PACKAGE LABEL

Hempvana

Maximum Strength Pain Relief Cream

Platinum

+4x Hemp* Seed Oil

For Moisturization

Trolamine Salicylate 10%

For Pain

Net Wt. 4 oz (119 g)

*Compared to original Hempvana Pain Relief Cream